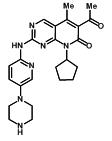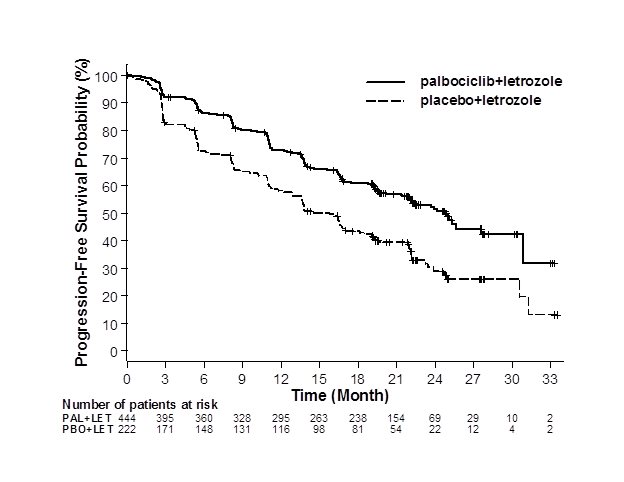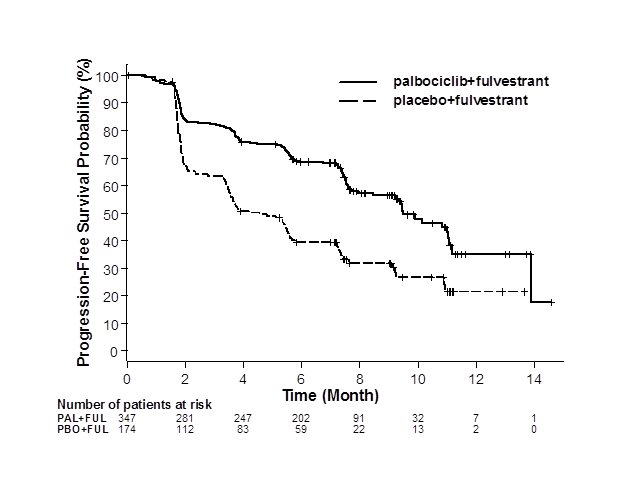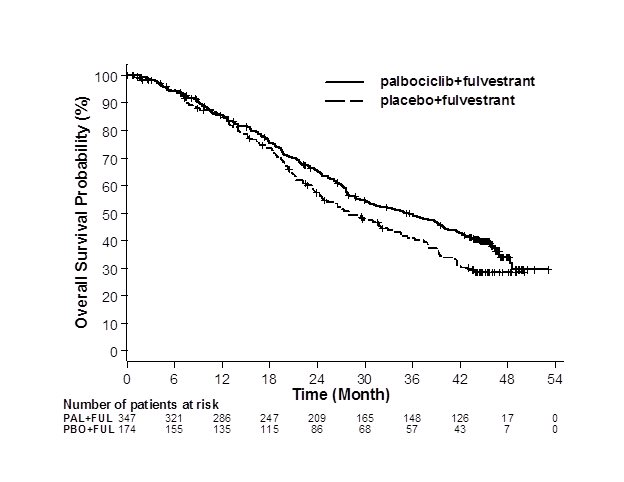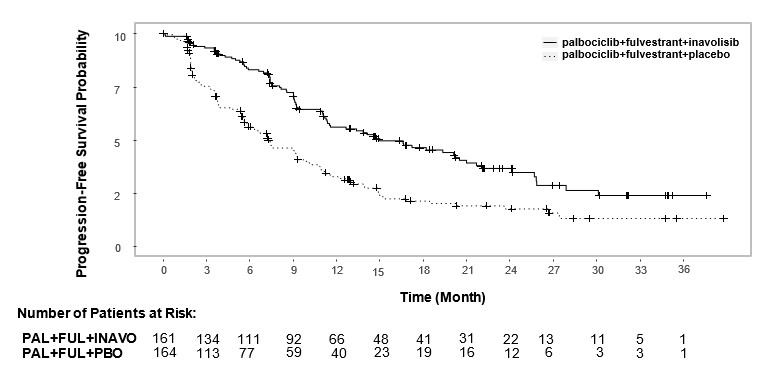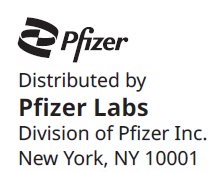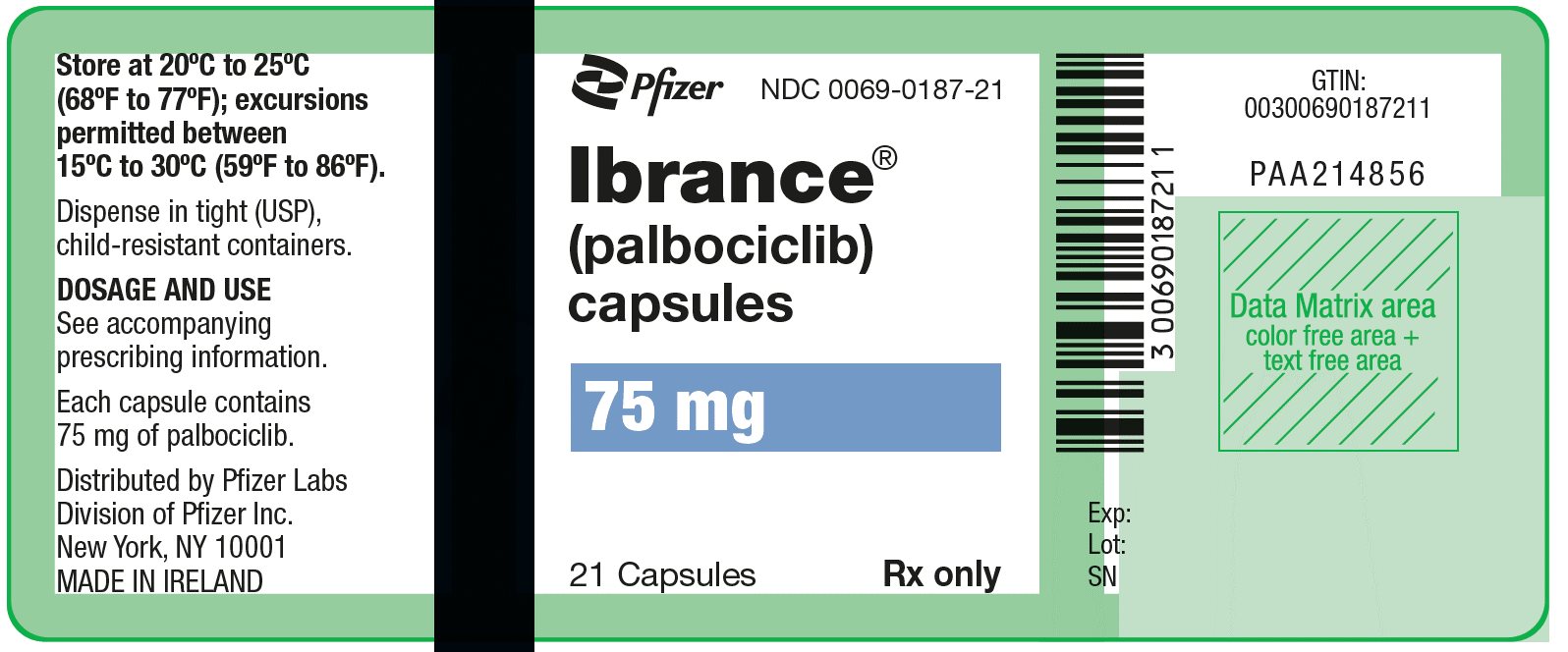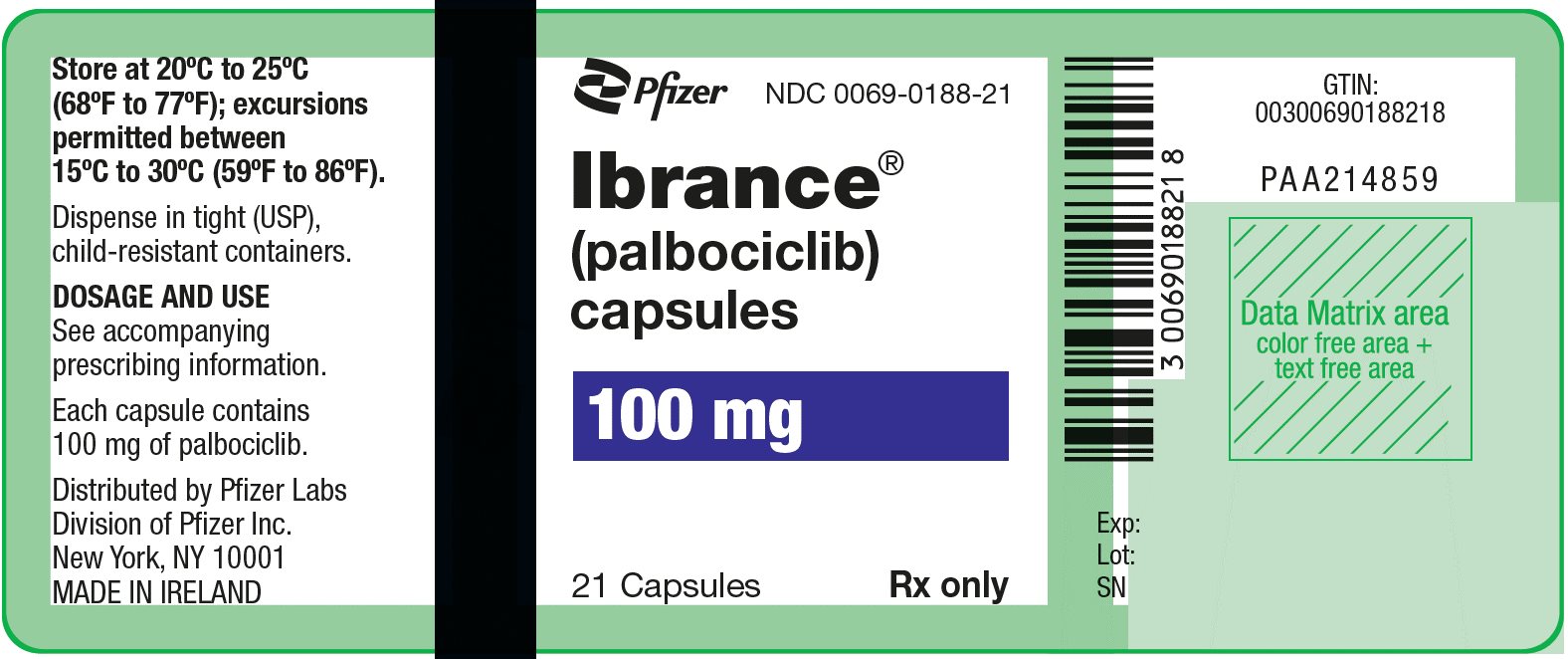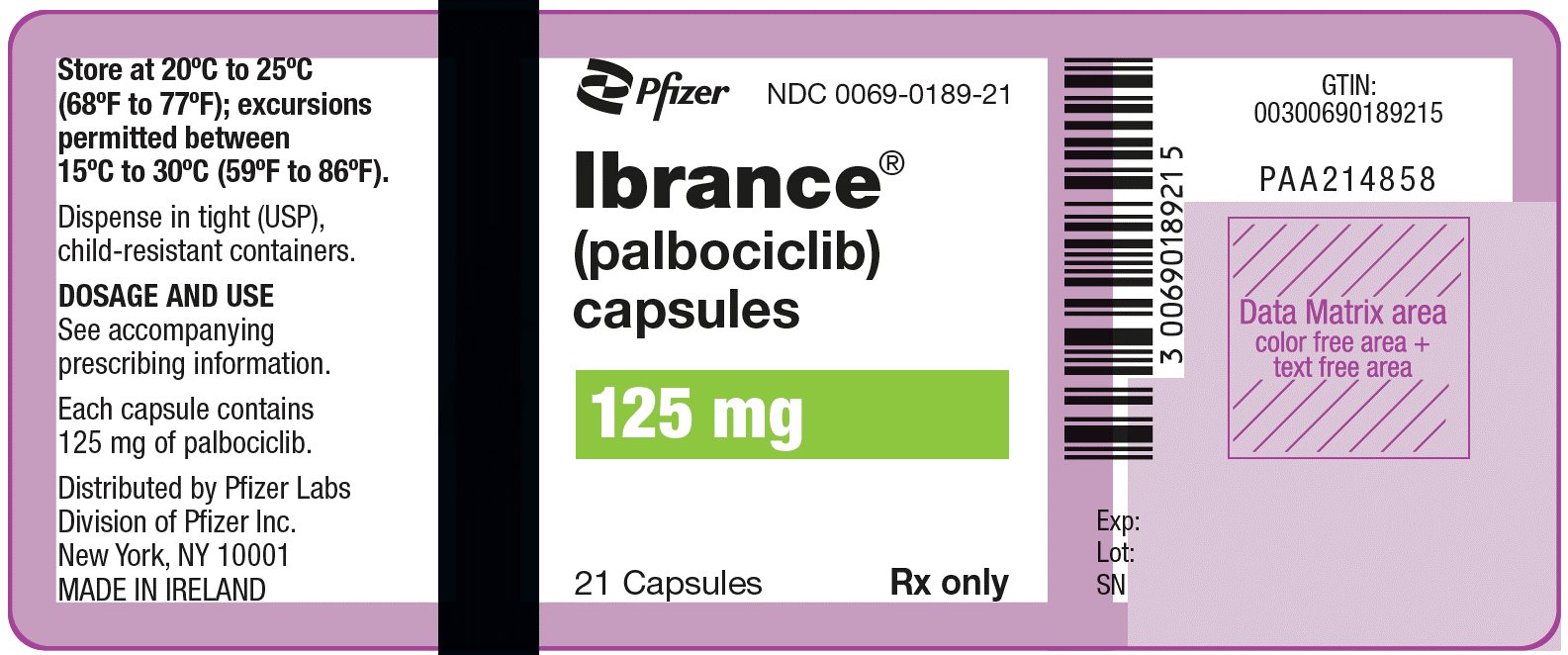 DRUG LABEL: Ibrance
NDC: 0069-0187 | Form: CAPSULE
Manufacturer: Pfizer Laboratories Div Pfizer Inc
Category: prescription | Type: HUMAN PRESCRIPTION DRUG LABEL
Date: 20251212

ACTIVE INGREDIENTS: PALBOCICLIB 75 mg/1 1
INACTIVE INGREDIENTS: MICROCRYSTALLINE CELLULOSE; LACTOSE MONOHYDRATE; SODIUM STARCH GLYCOLATE TYPE A POTATO; SILICON DIOXIDE; MAGNESIUM STEARATE; GELATIN, UNSPECIFIED; FERRIC OXIDE RED; FERRIC OXIDE YELLOW; TITANIUM DIOXIDE; SHELLAC; AMMONIA; PROPYLENE GLYCOL; DIMETHICONE

HIGHLIGHTS OF PRESCRIBING INFORMATION

These highlights do not include all the information needed to use IBRANCE safely and effectively. See full prescribing information for IBRANCE.
IBRANCE® (palbociclib) capsules, for oral use
Initial U.S. Approval: 2015

RECENT MAJOR CHANGES

Indications and Usage (1) | 4/2025
Dosage and Administration (2.1, 2.2) | 4/2025

1 INDICATIONS AND USAGE

IBRANCE is a kinase inhibitor indicated:

- for the treatment of adult patients with hormone receptor (HR)-positive, human epidermal growth factor receptor 2 (HER2)-negative advanced or metastatic breast cancer in combination with:
  - an aromatase inhibitor as initial endocrine-based therapy (1); or
  - fulvestrant in patients with disease progression following endocrine therapy. (1)
- in combination with inavolisib and fulvestrant for the treatment of adult patients with endocrine-resistant, PIK3CA-mutated, HR-positive, HER2-negative, locally advanced or metastatic breast cancer, as detected by an FDA-approved test, following recurrence on or after completing adjuvant endocrine therapy. (1)

2 DOSAGE AND ADMINISTRATION

IBRANCE capsules are taken orally with food in combination with an aromatase inhibitor, fulvestrant, or inavolisib and fulvestrant. (2)

- Recommended starting dose: 125 mg once daily taken with food for 21 days followed by 7 days off treatment. (2.1)
- Dosing interruption and/or dose reductions are recommended based on individual safety and tolerability. (2.2)

3 DOSAGE FORMS AND STRENGTHS

Capsules: 125 mg, 100 mg, and 75 mg. (3)

4 CONTRAINDICATIONS

None. (4)

5 WARNINGS AND PRECAUTIONS

- Neutropenia: Monitor complete blood count prior to start of IBRANCE therapy and at the beginning of each cycle, as well as on Day 15 of the first 2 cycles, and as clinically indicated. (2.2, 5.1)
- Interstitial Lung Disease (ILD)/Pneumonitis: Severe and fatal cases of ILD/pneumonitis have been reported. Monitor for pulmonary symptoms of ILD/pneumonitis. Interrupt IBRANCE immediately in patients with suspected ILD/pneumonitis. Permanently discontinue IBRANCE if severe ILD/pneumonitis occurs. (5.2)
- Embryo-Fetal Toxicity: IBRANCE can cause fetal harm. Advise patients of potential risk to a fetus and to use effective contraception. (5.3, 8.1, 8.3)

6 ADVERSE REACTIONS

Most common adverse reactions (incidence ≥20%) in combination with either letrozole or fulvestrant, including laboratory abnormalities, were white blood cell count decreased, neutrophils decreased, blood creatinine increased, hemoglobin decreased, platelets decreased, infections, aspartate aminotransferase increased, alanine aminotransferase increased, fatigue, nausea, stomatitis, diarrhea, and alopecia. (6.1)

The most common adverse reactions (incidence ≥20%) in combination with inavolisib and fulvestrant, including laboratory abnormalities, were neutrophils decreased, hemoglobin decreased, fasting glucose increased, platelets decreased, lymphocytes decreased, stomatitis, diarrhea, calcium decreased, fatigue, potassium decreased, creatinine increased, alanine aminotransferase (ALT) increased, nausea, sodium decreased, magnesium decreased, rash, decreased appetite, COVID-19 infection, and headache. (6.1)

To report SUSPECTED ADVERSE REACTIONS, contact Pfizer Inc at 1-800-438-1985 or FDA at 1-800-FDA-1088 or www.fda.gov/medwatch.

7 DRUG INTERACTIONS

- CYP3A Inhibitors: Avoid concurrent use of IBRANCE with strong CYP3A inhibitors. If the strong inhibitor cannot be avoided, reduce the IBRANCE dose. (2.2, 7.1)
- CYP3A Inducers: Avoid concurrent use of IBRANCE with strong CYP3A inducers. (7.2)
- CYP3A Substrates: The dose of sensitive CYP3A4 substrates with narrow therapeutic indices may need to be reduced when given concurrently with IBRANCE. (7.3)

8 USE IN SPECIFIC POPULATIONS

- Lactation: Advise not to breastfeed. (8.2)

FULL PRESCRIBING INFORMATION

1 INDICATIONS AND USAGE

IBRANCE is indicated for the treatment of adult patients with hormone receptor (HR)-positive, human epidermal growth factor receptor 2 (HER2)-negative advanced or metastatic breast cancer in combination with:

- an aromatase inhibitor as initial endocrine-based therapy; or
- fulvestrant in patients with disease progression following endocrine therapy.

IBRANCE is indicated in combination with inavolisib and fulvestrant for the treatment of adult patients with endocrine-resistant, PIK3CA-mutated, HR-positive, HER2-negative, locally advanced or metastatic breast cancer, as detected by an FDA-approved test, following recurrence on or after completing adjuvant endocrine therapy.

2 DOSAGE AND ADMINISTRATION

2.1 Recommended Dose and Schedule

The recommended dose of IBRANCE is a 125 mg capsule taken orally once daily for 21 consecutive days followed by 7 days off treatment to comprise a complete cycle of 28 days. IBRANCE capsule should be taken with food [see Clinical Pharmacology (12.3)].

Administer the recommended dose of an aromatase inhibitor when given with IBRANCE. Please refer to the Full Prescribing Information for the aromatase inhibitor being used.

When given with IBRANCE, the recommended dose of fulvestrant is 500 mg administered on Days 1, 15, 29, and once monthly thereafter. Please refer to the Full Prescribing Information of fulvestrant.

Refer to the Full Prescribing Information for inavolisib and fulvestrant for dosing information.

Advise patients to take their dose of IBRANCE at approximately the same time each day.

If the patient vomits or misses a dose, an additional dose should not be taken. The next prescribed dose should be taken at the usual time. IBRANCE capsules should be swallowed whole (do not chew, crush, or open them prior to swallowing). Capsules should not be ingested if they are broken, cracked, or otherwise not intact.

Pre/perimenopausal women treated with the combination IBRANCE plus an aromatase inhibitor or fulvestrant or IBRANCE plus inavolisib and fulvestrant therapy should also be treated with luteinizing hormone-releasing hormone (LHRH) agonists according to current clinical practice standards.

For men treated with combination IBRANCE plus aromatase inhibitor or IBRANCE plus inavolisib and fulvestrant therapy, consider treatment with an LHRH agonist according to current clinical practice standards.

2.2 Dose Modification

The recommended dose modifications for adverse reactions are listed in Tables 1, 2, and 3.

Table 1. Recommended Dose Modification for Adverse Reactions
Dose Level | Dose
Recommended starting dose | 125 mg/day
First dose reduction | 100 mg/day
Second dose reduction | 75 mg/day [If further dose reduction below 75 mg/day is required, discontinue.]

Table 2. Dose Modification and Management – Hematologic Toxicities [Table applies to all hematologic adverse reactions except lymphopenia (unless associated with clinical events, e.g., opportunistic infections).]
Monitor complete blood counts prior to the start of IBRANCE therapy and at the beginning of each cycle, as well as on Day 15 of the first 2 cycles, and as clinically indicated.
For patients who experience a maximum of Grade 1 or 2 neutropenia in the first 6 cycles, monitor complete blood counts for subsequent cycles every 3 months, prior to the beginning of a cycle and as clinically indicated.
CTCAE Grade | Dose Modifications
Grade 1 or 2 | No dose adjustment is required.
Grade 3 | Day 1 of cycle: Withhold IBRANCE, repeat complete blood count monitoring within 1 week. When recovered to Grade ≤2, start the next cycle at the same dose. Day 15 of first 2 cycles: If Grade 3 on Day 15, continue IBRANCE at current dose to complete cycle and repeat complete blood count on Day 22. If Grade 4 on Day 22, see Grade 4 dose modification guidelines below. Consider dose reduction in cases of prolonged (>1 week) recovery from Grade 3 neutropenia or recurrent Grade 3 neutropenia on Day 1 of subsequent cycles.
Grade 3 neutropenia [Absolute neutrophil count (ANC): Grade 1: ANC < LLN - 1500/mm^3; Grade 2: ANC 1000 - <1500/mm^3; Grade 3: ANC 500 - <1000/mm^3; Grade 4: ANC <500/mm^3.] with fever ≥38.5 ºC and/or infection | At any time: Withhold IBRANCE until recovery to Grade ≤2. Resume at the next lower dose.
Grade 4 | At any time: Withhold IBRANCE until recovery to Grade ≤2. Resume at the next lower dose.
Grading according to CTCAE 4.0.
CTCAE=Common Terminology Criteria for Adverse Events; LLN=lower limit of normal.

Table 3. Dose Modification and Management – Non-Hematologic Toxicities
CTCAE Grade | Dose Modifications
Grade 1 or 2 | No dose adjustment is required.
Grade ≥3 non-hematologic toxicity (if persisting despite optimal medical treatment) | Withhold until symptoms resolve to:; - Grade ≤1; - Grade ≤2 (if not considered a safety risk for the patient); Resume at the next lower dose.
Grading according to CTCAE 4.0.
CTCAE=Common Terminology Criteria for Adverse Events.

Permanently discontinue IBRANCE in patients with severe interstitial lung disease (ILD)/pneumonitis.

Refer to the Full Prescribing Information for coadministered endocrine therapy and/or inavolisib dose adjustment guidelines in the event of toxicity and other relevant safety information or contraindications.

Dose Modifications for Use With Strong CYP3A Inhibitors

Avoid concomitant use of strong CYP3A inhibitors and consider an alternative concomitant medication with no or minimal CYP3A inhibition. If patients must be coadministered a strong CYP3A inhibitor, reduce the IBRANCE dose to 75 mg once daily. If the strong inhibitor is discontinued, increase the IBRANCE dose (after 3 to 5 half-lives of the inhibitor) to the dose used prior to the initiation of the strong CYP3A inhibitor [see Drug Interactions (7.1) and Clinical Pharmacology (12.3)].

Dose Modifications for Hepatic Impairment

No dose adjustment is required for patients with mild or moderate hepatic impairment (Child-Pugh classes A and B). For patients with severe hepatic impairment (Child-Pugh class C), the recommended dose of IBRANCE is 75 mg once daily for 21 consecutive days followed by 7 days off treatment to comprise a complete cycle of 28 days [see Use in Specific Populations (8.6) and Clinical Pharmacology (12.3)].

3 DOSAGE FORMS AND STRENGTHS

125 mg capsules: opaque, hard gelatin capsules, size 0, with caramel cap and body, printed with white ink "Pfizer" on the cap, "PBC 125" on the body.

100 mg capsules: opaque, hard gelatin capsules, size 1, with caramel cap and light orange body, printed with white ink "Pfizer" on the cap, "PBC 100" on the body.

75 mg capsules: opaque, hard gelatin capsules, size 2, with light orange cap and body, printed with white ink "Pfizer" on the cap, "PBC 75" on the body.

4 CONTRAINDICATIONS

None.

5 WARNINGS AND PRECAUTIONS

5.1 Neutropenia

Neutropenia was the most frequently reported adverse reaction in PALOMA-2 with an incidence of 80% and PALOMA-3 with an incidence of 83%. A Grade ≥3 decrease in neutrophil counts was reported in 66% of patients receiving IBRANCE plus letrozole in PALOMA-2 and 66% of patients receiving IBRANCE plus fulvestrant in PALOMA-3. In PALOMA-2 and PALOMA-3, the median time to first episode of any grade neutropenia was 15 days and the median duration of Grade ≥3 neutropenia was 7 days [see Adverse Reactions (6.1)].

Monitor complete blood counts prior to starting IBRANCE therapy and at the beginning of each cycle, as well as on Day 15 of the first 2 cycles, and as clinically indicated. Dose interruption, dose reduction, or delay in starting treatment cycles is recommended for patients who develop Grade 3 or 4 neutropenia [see Dosage and Administration (2.2)].

Febrile neutropenia has been reported in 1.8% of patients exposed to IBRANCE across PALOMA-2 and PALOMA-3. One death due to neutropenic sepsis was observed in PALOMA-3. Physicians should inform patients to promptly report any episodes of fever [see Patient Counseling Information (17)].

5.2 Interstitial Lung Disease (ILD)/Pneumonitis

Severe, life-threatening, or fatal interstitial lung disease (ILD) and/or pneumonitis can occur in patients treated with cyclin-dependent kinase 4/6 (CDK4/6) inhibitors, including IBRANCE when taken in combination with endocrine therapy.

Across clinical trials (PALOMA-1, PALOMA-2, PALOMA-3), 1% of IBRANCE-treated patients had ILD/pneumonitis of any grade, 0.1% had Grade 3 or 4 and no fatal cases were reported. Additional cases of ILD/pneumonitis have been observed in the postmarketing setting, with fatalities reported [see Adverse Reactions (6.2)].

Monitor patients for pulmonary symptoms indicative of ILD/pneumonitis (e.g. hypoxia, cough, dyspnea). In patients who have new or worsening respiratory symptoms and are suspected to have developed pneumonitis, interrupt IBRANCE immediately and evaluate the patient. Permanently discontinue IBRANCE in patients with severe ILD or pneumonitis [see Dosage and Administration (2.2)].

5.3 Embryo-Fetal Toxicity

Based on findings from animal studies and its mechanism of action, IBRANCE can cause fetal harm when administered to a pregnant woman. In animal reproduction studies, administration of palbociclib to pregnant rats and rabbits during organogenesis resulted in embryo-fetal toxicity at maternal exposures that were ≥4 times the human clinical exposure based on area under the curve (AUC). Advise pregnant women of the potential risk to a fetus. Advise females of reproductive potential to use effective contraception during treatment with IBRANCE and for at least 3 weeks after the last dose [see Use in Specific Populations (8.1 and 8.3) and Clinical Pharmacology (12.1)].

6 ADVERSE REACTIONS

The following clinically significant adverse reactions are described elsewhere in the labeling:

- Neutropenia [see Warnings and Precautions (5.1)]
- ILD/Pneumonitis [see Warnings and Precautions (5.2)]

6.1 Clinical Studies Experience

Because clinical trials are conducted under widely varying conditions, adverse reaction rates observed in the clinical trials of a drug cannot be directly compared to rates in the clinical trials of another drug and may not reflect the rates observed in practice.

PALOMA-2: IBRANCE plus Letrozole

Patients with estrogen receptor (ER)-positive, HER2-negative advanced or metastatic breast cancer for initial endocrine-based therapy

The safety of IBRANCE (125 mg/day) plus letrozole (2.5 mg/day) versus placebo plus letrozole was evaluated in PALOMA-2. The data described below reflect exposure to IBRANCE in 444 out of 666 patients with ER-positive, HER2-negative advanced breast cancer who received at least 1 dose of IBRANCE plus letrozole in PALOMA-2. The median duration of treatment for IBRANCE plus letrozole was 19.8 months while the median duration of treatment for placebo plus letrozole arm was 13.8 months.

Dose reductions due to an adverse reaction of any grade occurred in 36% of patients receiving IBRANCE plus letrozole. No dose reduction was allowed for letrozole in PALOMA-2.

Permanent discontinuation associated with an adverse reaction occurred in 43 of 444 (10%) patients receiving IBRANCE plus letrozole and in 13 of 222 (6%) patients receiving placebo plus letrozole. Adverse reactions leading to permanent discontinuation for patients receiving IBRANCE plus letrozole included neutropenia (1.1%) and alanine aminotransferase increase (0.7%).

The most common adverse reactions (≥10%) of any grade reported in patients in the IBRANCE plus letrozole arm by descending frequency were neutropenia, infections, leukopenia, fatigue, nausea, alopecia, stomatitis, diarrhea, anemia, rash, asthenia, thrombocytopenia, vomiting, decreased appetite, dry skin, pyrexia, and dysgeusia.

The most frequently reported Grade ≥3 adverse reactions (≥5%) in patients receiving IBRANCE plus letrozole by descending frequency were neutropenia, leukopenia, infections, and anemia.

Adverse reactions (≥10%) reported in patients who received IBRANCE plus letrozole or placebo plus letrozole in PALOMA-2 are listed in Table 4.

Table 4. Adverse Reactions (≥10%) in PALOMA-2
 | IBRANCE plus Letrozole (N=444) |  |  | Placebo plus Letrozole (N=222)
Adverse Reaction | All Grades % | Grade 3 % | Grade 4 % | All Grades % | Grade 3 % | Grade 4 %
Infections and infestations
Infections [Infections includes all reported preferred terms (PTs) that are part of the System Organ Class Infections and infestations.] | 60 [Most common infections (≥1%) include: nasopharyngitis, upper respiratory tract infection, urinary tract infection, oral herpes, sinusitis, rhinitis, bronchitis, influenza, pneumonia, gastroenteritis, conjunctivitis, herpes zoster, pharyngitis, cellulitis, cystitis, lower respiratory tract infection, tooth infection, gingivitis, skin infection, gastroenteritis viral, respiratory tract infection, respiratory tract infection viral, and folliculitis.] | 6 | 1 | 42 | 3 | 0
Blood and lymphatic system disorders
Neutropenia | 80 | 56 | 10 | 6 | 1 | 1
Leukopenia | 39 | 24 | 1 | 2 | 0 | 0
Anemia | 24 | 5 | <1 | 9 | 2 | 0
Thrombocytopenia | 16 | 1 | <1 | 1 | 0 | 0
Metabolism and nutrition disorders
Decreased appetite | 15 | 1 | 0 | 9 | 0 | 0
Nervous system disorders
Dysgeusia | 10 | 0 | 0 | 5 | 0 | 0
Gastrointestinal disorders
Stomatitis [Stomatitis includes: aphthous stomatitis, cheilitis, glossitis, glossodynia, mouth ulceration, mucosal inflammation, oral pain, oral discomfort, oropharyngeal pain, and stomatitis.] | 30 | 1 | 0 | 14 | 0 | 0
Nausea | 35 | <1 | 0 | 26 | 2 | 0
Diarrhea | 26 | 1 | 0 | 19 | 1 | 0
Vomiting | 16 | 1 | 0 | 17 | 1 | 0
Skin and subcutaneous tissue disorders
Alopecia | 33 [Grade 1 events – 30%; Grade 2 events – 3%.] | N/A | N/A | 16 [Grade 1 events – 15%; Grade 2 events – 1%.] | N/A | N/A
Rash [Rash includes the following PTs: rash, rash maculo-papular, rash pruritic, rash erythematous, rash papular, dermatitis, dermatitis acneiform, and toxic skin eruption.] | 18 | 1 | 0 | 12 | 1 | 0
Dry skin | 12 | 0 | 0 | 6 | 0 | 0
General disorders and administration site conditions
Fatigue | 37 | 2 | 0 | 28 | 1 | 0
Asthenia | 17 | 2 | 0 | 12 | 0 | 0
Pyrexia | 12 | 0 | 0 | 9 | 0 | 0
Grading according to CTCAE 4.0.
CTCAE=Common Terminology Criteria for Adverse Events; N=number of patients; N/A=not applicable;

Clinically relevant adverse reactions in <10% of patients who received IBRANCE plus letrozole in PALOMA-2 included epistaxis (9%), lacrimation increased (6%), dry eye (4.1%), vision blurred (3.6%), and febrile neutropenia (2.5%).

Table 5. Laboratory Abnormalities in PALOMA-2
 | IBRANCE plus Letrozole (N=444) |  |  | Placebo plus Letrozole (N=222)
Laboratory Abnormality | All Grades % | Grade 3 % | Grade 4 % | All Grades % | Grade 3 % | Grade 4 %
WBC decreased | 97 | 35 | 1 | 25 | 1 | 0
Blood creatinine increased | 96 | 2 | <1 | 91 | 0 | 0
Neutrophils decreased | 95 | 56 | 12 | 20 | 1 | 1
Hemoglobin decreased | 78 | 6 | 0 | 42 | 2 | 0
Platelets decreased | 63 | 1 | 1 | 14 | 0 | 0
Aspartate aminotransferase increased | 52 | 3 | 0 | 34 | 1 | 0
Alanine aminotransferase increased | 43 | 2 | <1 | 30 | 0 | 0
N=number of patients; WBC=white blood cells.

PALOMA-3: IBRANCE plus Fulvestrant

Patients with HR-positive, HER2-negative advanced or metastatic breast cancer who have had disease progression on or after prior adjuvant or metastatic endocrine therapy

The safety of IBRANCE (125 mg/day) plus fulvestrant (500 mg) versus placebo plus fulvestrant was evaluated in PALOMA-3. The data described below reflect exposure to IBRANCE in 345 out of 517 patients with HR-positive, HER2-negative advanced or metastatic breast cancer who received at least 1 dose of IBRANCE plus fulvestrant in PALOMA-3. The median duration of treatment for IBRANCE plus fulvestrant was 10.8 months while the median duration of treatment for placebo plus fulvestrant arm was 4.8 months.

Dose reductions due to an adverse reaction of any grade occurred in 36% of patients receiving IBRANCE plus fulvestrant. No dose reduction was allowed for fulvestrant in PALOMA-3.

Permanent discontinuation associated with an adverse reaction occurred in 19 of 345 (6%) patients receiving IBRANCE plus fulvestrant, and in 6 of 172 (3%) patients receiving placebo plus fulvestrant. Adverse reactions leading to discontinuation for those patients receiving IBRANCE plus fulvestrant included fatigue (0.6%), infections (0.6%), and thrombocytopenia (0.6%).

The most common adverse reactions (≥10%) of any grade reported in patients in the IBRANCE plus fulvestrant arm by descending frequency were neutropenia, leukopenia, infections, fatigue, nausea, anemia, stomatitis, diarrhea, thrombocytopenia, vomiting, alopecia, rash, decreased appetite, and pyrexia.

The most frequently reported Grade ≥3 adverse reactions (≥5%) in patients receiving IBRANCE plus fulvestrant in descending frequency were neutropenia and leukopenia.

Adverse reactions (≥10%) reported in patients who received IBRANCE plus fulvestrant or placebo plus fulvestrant in PALOMA-3 are listed in Table 6.

Table 6. Adverse Reactions (≥10%) in PALOMA-3
Adverse Reaction | IBRANCE plus Fulvestrant (N=345) |  |  | Placebo plus Fulvestrant (N=172)
Adverse Reaction | All Grades | Grade 3 | Grade 4 | All Grades | Grade 3 | Grade 4
Adverse Reaction | % | % | % | % | % | %
Infections and infestations
Infections [Infections includes all reported preferred terms (PTs) that are part of the System Organ Class Infections and infestations.] | 47 [Most common infections (≥1%) include: nasopharyngitis, upper respiratory infection, urinary tract infection, bronchitis, rhinitis, influenza, conjunctivitis, sinusitis, pneumonia, cystitis, oral herpes, respiratory tract infection, gastroenteritis, tooth infection, pharyngitis, eye infection, herpes simplex, and paronychia.] | 3 | 1 | 31 | 3 | 0
Blood and lymphatic system disorders
Neutropenia | 83 | 55 | 11 | 4 | 1 | 0
Leukopenia | 53 | 30 | 1 | 5 | 1 | 1
Anemia | 30 | 4 | 0 | 13 | 2 | 0
Thrombocytopenia | 23 | 2 | 1 | 0 | 0 | 0
Metabolism and nutrition disorders
Decreased appetite | 16 | 1 | 0 | 8 | 1 | 0
Gastrointestinal disorders
Nausea | 34 | 0 | 0 | 28 | 1 | 0
Stomatitis [Stomatitis includes: aphthous stomatitis, cheilitis, glossitis, glossodynia, mouth ulceration, mucosal inflammation, oral pain, oropharyngeal discomfort, oropharyngeal pain, stomatitis.] | 28 | 1 | 0 | 13 | 0 | 0
Diarrhea | 24 | 0 | 0 | 19 | 1 | 0
Vomiting | 19 | 1 | 0 | 15 | 1 | 0
Skin and subcutaneous tissue disorders
Alopecia | 18 [Grade 1 events – 17%; Grade 2 events – 1%.] | N/A | N/A | 6 [Grade 1 events – 6%.] | N/A | N/A
Rash [Rash includes: rash, rash maculo-papular, rash pruritic, rash erythematous, rash papular, dermatitis, dermatitis acneiform, toxic skin eruption.] | 17 | 1 | 0 | 6 | 0 | 0
General disorders and administration site conditions
Fatigue | 41 | 2 | 0 | 29 | 1 | 0
Pyrexia | 13 | <1 | 0 | 5 | 0 | 0
Grading according to CTCAE 4.0.
CTCAE=Common Terminology Criteria for Adverse Events; N=number of patients; N/A=not applicable.

Clinically relevant adverse reactions in <10% of patients who received IBRANCE plus fulvestrant in PALOMA-3 included asthenia (8%), dysgeusia (7%), epistaxis (7%), lacrimation increased (6%), dry skin (6%), vision blurred (6%), dry eye (3.8%), and febrile neutropenia (0.9%).

Table 7. Laboratory Abnormalities in PALOMA-3
Laboratory Abnormality | IBRANCE plus Fulvestrant (N=345) |  |  | Placebo plus Fulvestrant (N=172)
Laboratory Abnormality | All Grades % | Grade 3 % | Grade 4 % | All Grades % | Grade 3 % | Grade 4 %
WBC decreased | 99 | 45 | 1 | 26 | 0 | 1
Neutrophils decreased | 96 | 56 | 11 | 14 | 0 | 1
Blood creatinine increased | 95 | 1 | 0 | 82 | 0 | 0
Hemoglobin decreased | 78 | 3 | 0 | 40 | 2 | 0
Platelets decreased | 62 | 2 | 1 | 10 | 0 | 0
Aspartate aminotransferase increased | 43 | 4 | 0 | 48 | 4 | 0
Alanine aminotransferase increased | 36 | 2 | 0 | 34 | 0 | 0
N=number of patients; WBC=white blood cells.

INAVO120: IBRANCE plus Inavolisib and Fulvestrant

Adults with PIK3CA-mutated, HR-positive, HER2-negative, locally advanced or metastatic breast cancer whose disease progressed during or within 12 months of completing adjuvant endocrine therapy and who have not received prior systemic therapy for locally advanced or metastatic disease

The safety of the combination of IBRANCE plus inavolisib and fulvestrant was evaluated in a randomized, double-blind, placebo-controlled study (INAVO120) in 324 patients with PIK3CA-mutated, HR-positive, HER2-negative, locally advanced or metastatic breast cancer [see Clinical Studies (14)].

Patients received either IBRANCE 125 mg orally once daily for 21 consecutive days followed by 7 days off treatment to comprise a cycle of 28 days plus fulvestrant in combination with inavolisib (n=162) or placebo (n=162). The median duration of treatment for IBRANCE plus inavolisib and fulvestrant was 9 months (range: 0 to 39 months).

Serious adverse reactions occurred in 24% of patients who received IBRANCE plus inavolisib and fulvestrant. Serious adverse reactions occurring in ≥1% of patients receiving IBRANCE plus inavolisib and fulvestrant included anemia (1.9%), diarrhea (1.2%), and urinary tract infection (1.2%).

Fatal adverse reactions occurred in 3.7% of patients who received IBRANCE plus inavolisib and fulvestrant, including (0.6% each) acute coronary syndrome, cerebral hemorrhage, cerebrovascular accident, COVID-19 infection, and gastrointestinal hemorrhage.

Permanent discontinuation of IBRANCE associated with an adverse reaction occurred in 8 of 162 (4.9%) patients receiving IBRANCE plus inavolisib and fulvestrant and in 0 of 162 patients receiving IBRANCE plus placebo and fulvestrant. Adverse reactions leading to discontinuation of IBRANCE in patients receiving IBRANCE plus inavolisib and fulvestrant were neutropenia, infections, alanine aminotransferase increased, gastric ulcer, intestinal perforation, hyperglycemia, type 2 diabetes mellitus, bone pain, musculoskeletal pain, transitional cell carcinoma, and acute kidney injury (0.6% each).

Dose reduction of IBRANCE due to an adverse reaction occurred in 38% of patients receiving IBRANCE plus inavolisib and fulvestrant and in 30% of patients receiving IBRANCE plus placebo and fulvestrant. Adverse reactions leading to dose reductions of IBRANCE in ≥2% patients receiving IBRANCE plus inavolisib and fulvestrant were neutropenia (30%), leukopenia (6%), and thrombocytopenia (3.7%).

Dose interruption of IBRANCE due to an adverse reaction occurred in 71% of patients receiving IBRANCE plus inavolisib and fulvestrant and in 61% of patients receiving IBRANCE plus placebo and fulvestrant. Adverse reactions leading to dose interruption of IBRANCE in ≥2% patients receiving IBRANCE plus inavolisib and fulvestrant were neutropenia (56%), infections (29%), leukopenia (12%), stomatitis (4.9%), anemia (6%), thrombocytopenia (4.3%), diarrhea (3.7%), pyrexia (3.1%), alanine aminotransferase increased (2.5%), hyperglycemia (2.5%), and nausea (2.5%).

The most common (≥20%) adverse reactions, including laboratory abnormalities, were decreased neutrophils, decreased hemoglobin, increased fasting glucose, decreased platelets, decreased lymphocytes, stomatitis, diarrhea, decreased calcium, fatigue, decreased potassium, increased creatinine, increased alanine aminotransferase (ALT), nausea, decreased sodium, decreased magnesium, rash, decreased appetite, COVID-19 infection, and headache.

Adverse reactions and laboratory abnormalities in INAVO120 are summarized in Table 8 and Table 9, respectively.

Table 8. Adverse Reactions (≥10% with ≥5% [All Grades] or ≥2% [Grade 3-4] Higher Incidence in the IBRANCE plus inavolisib and fulvestrant Arm) in INAVO120
Adverse Reaction | IBRANCE plus Inavolisib and Fulvestrant (N=162) |  | IBRANCE plus Placebo and Fulvestrant (N=162)
Adverse Reaction | All Grades (%) | Grade 3-4 (%) | All Grades (%) | Grade 3-4 (%)
Gastrointestinal Disorders
Stomatitis [Includes aphthous ulcer, glossitis, glossodynia, lip ulceration, mouth ulceration, mucosal inflammation, and stomatitis.] | 51 | 6 [No Grade 4 adverse reactions were observed.] | 27 | 0
Diarrhea | 48 | 3.7 | 16 | 0
Nausea | 28 | 0.6 | 17 | 0
Vomiting | 15 | 0.6 | 4.9 | 1.2
General Disorders and Administration Site Conditions
Fatigue | 38 | 1.9 | 25 | 1.2
Skin and Subcutaneous Tissue Disorders
Rash [Includes other related terms.] | 26 | 0 | 19 | 0
Alopecia | 19 | 0 | 6 | 0
Dry skin [Includes dry skin, skin fissures, xerosis, and xeroderma.] | 13 | 0 | 4.3 | 0
Metabolism and Nutrition Disorders
Decreased appetite | 24 | 0 | 9 | 0
Infections and Infestations
COVID-19 infection | 23 | 1.9 | 10 | 0.6
Urinary tract infection | 15 | 1.2 | 9 | 0
Nervous System Disorders
Headache | 22 | 0 | 14 | 0
Investigations
Decreased weight | 17 | 3.7 | 0.6 | 0

Clinically relevant adverse reactions occurring in <10% of patients who received the triplet combination of IBRANCE plus inavolisib and fulvestrant included abdominal pain, dry eye, dysgeusia, and dyspepsia.

Table 9. Select Laboratory Abnormalities (≥10% with a ≥2% [All Grades or Grade 3-4] Higher Incidence in the IBRANCE plus Inavolisib and Fulvestrant Arm) in INAVO120
Laboratory Abnormality | IBRANCE plus Inavolisib and Fulvestrant [The denominator used to calculate the rate varied from 122 to 160 based on the number of patients with a baseline value and at least one post-treatment value.] |  | IBRANCE plus Placebo and Fulvestrant [The denominator used to calculate the rate varied from 131 to 161 based on the number of patients with a baseline value and at least one post-treatment value.]
Laboratory Abnormality | All Grades (%) | Grade 3-4 (%) | All Grades (%) | Grade 3-4 (%)
Hematology
Neutrophils (total, absolute) decreased | 95 | 82 | 97 | 79
Hemoglobin decreased | 88 | 8 [No Grade 4 laboratory abnormalities were observed.] | 85 | 2.5
Platelets decreased | 8 | 16 | 71 | 3.7
Lymphocytes (absolute) decreased | 72 | 9 | 68 | 14
Chemistry
Glucose (fasting) increased [Grading according to CTCAE version 4.03.] | 85 | 12 | 43 | 0
Calcium decreased | 42 | 3.1 | 32 | 3.7
Potassium decreased | 38 | 6 | 21 | 0.6
Creatinine increased | 38 | 1.9 | 30 | 1.2
ALT increased | 34 | 3.1 | 29 | 1.2
Sodium decreased | 28 | 2.5 | 19 | 2.5
Magnesium decreased | 27 | 0.6 | 21 | 0
Lipase (fasting) increased | 16 | 1.4 | 7 | 0
ALT=alanine aminotransferase.

Other Clinical Trials Experience

The following adverse reaction has been reported following administration of IBRANCE: venous thromboembolism.

6.2 Postmarketing Experience

The following adverse reactions have been identified during post-approval use of IBRANCE. Because these reactions are reported voluntarily from a population of uncertain size, it is not always possible to reliably estimate their frequency or establish a causal relationship to drug exposure.

Respiratory Disorders: Interstitial lung disease (ILD)/non-infectious pneumonitis

Skin and Subcutaneous Tissue Disorders: Palmar-plantar erythrodysesthesia syndrome (PPES)

Male Patients with HR-Positive, HER2-Negative Advanced or Metastatic Breast Cancer

Based on limited data from postmarketing reports and electronic health records, the safety profile for men treated with IBRANCE is consistent with the safety profile in women treated with IBRANCE.

7 DRUG INTERACTIONS

Palbociclib is primarily metabolized by CYP3A and sulfotransferase (SULT) enzyme SULT2A1. In vivo, palbociclib is a time-dependent inhibitor of CYP3A.

7.1 Agents That May Increase Palbociclib Plasma Concentrations

Effect of CYP3A Inhibitors

Coadministration of a strong CYP3A inhibitor (itraconazole) increased the plasma exposure of palbociclib in healthy subjects by 87%. Avoid concomitant use of strong CYP3A inhibitors (e.g., clarithromycin, indinavir, itraconazole, ketoconazole, lopinavir/ritonavir, nefazodone, nelfinavir, posaconazole, ritonavir, saquinavir, telaprevir, telithromycin, and voriconazole). Avoid grapefruit or grapefruit juice during IBRANCE treatment. If coadministration of IBRANCE with a strong CYP3A inhibitor cannot be avoided, reduce the dose of IBRANCE [see Dosage and Administration (2.2) and Clinical Pharmacology (12.3)].

7.2 Agents That May Decrease Palbociclib Plasma Concentrations

Effect of CYP3A Inducers

Coadministration of a strong CYP3A inducer (rifampin) decreased the plasma exposure of palbociclib in healthy subjects by 85%. Avoid concomitant use of strong CYP3A inducers (e.g., phenytoin, rifampin, carbamazepine, enzalutamide, and St John's Wort) [see Clinical Pharmacology (12.3)].

7.3 Drugs That May Have Their Plasma Concentrations Altered by Palbociclib

Coadministration of midazolam with multiple doses of IBRANCE increased the midazolam plasma exposure by 61%, in healthy subjects, compared to administration of midazolam alone. The dose of the sensitive CYP3A substrate with a narrow therapeutic index (e.g., alfentanil, cyclosporine, dihydroergotamine, ergotamine, everolimus, fentanyl, pimozide, quinidine, sirolimus, and tacrolimus) may need to be reduced, as IBRANCE may increase its exposure [see Clinical Pharmacology (12.3)].

8 USE IN SPECIFIC POPULATIONS

8.1 Pregnancy

Risk Summary

Based on findings from animal studies and its mechanism of action, IBRANCE can cause fetal harm when administered to a pregnant woman [see Clinical Pharmacology (12.1)]. There are no available data in pregnant women to inform the drug-associated risk. In animal reproduction studies, administration of palbociclib to pregnant rats and rabbits during organogenesis resulted in embryo-fetal toxicity at maternal exposures that were ≥4 times the human clinical exposure based on AUC (see Data). Advise pregnant women of the potential risk to a fetus.

The estimated background risk of major birth defects and miscarriage for the indicated population is unknown. In the U.S. general population, the estimated background risk of major birth defects and miscarriage in clinically recognized pregnancies is 2%–4% and 15%–20%, respectively.

Data

Animal Data

In a fertility and early embryonic development study in female rats, palbociclib was administered orally for 15 days before mating through to Day 7 of pregnancy, which did not cause embryo toxicity at doses up to 300 mg/kg/day with maternal systemic exposures approximately 4 times the human exposure (AUC) at the recommended dose.

In embryo-fetal development studies in rats and rabbits, pregnant animals received oral doses of palbociclib up to 300 mg/kg/day and 20 mg/kg/day, respectively, during the period of organogenesis. The maternally toxic dose of 300 mg/kg/day was fetotoxic in rats, resulting in reduced fetal body weights. At doses ≥100 mg/kg/day in rats, there was an increased incidence of a skeletal variation (increased incidence of a rib present at the seventh cervical vertebra). At the maternally toxic dose of 20 mg/kg/day in rabbits, there was an increased incidence of skeletal variations, including small phalanges in the forelimb. At 300 mg/kg/day in rats and 20 mg/kg/day in rabbits, the maternal systemic exposures were approximately 4 and 9 times the human exposure (AUC) at the recommended dose, respectively.

CDK4/6 double knockout mice have been reported to die in late stages of fetal development (gestation Day 14.5 until birth) due to severe anemia. However, knockout mouse data may not be predictive of effects in humans due to differences in degree of target inhibition.

8.2 Lactation

Risk Summary

There is no information regarding the presence of palbociclib in human milk, its effects on milk production, or the breastfed infant. Because of the potential for serious adverse reactions in breastfed infants from IBRANCE, advise a lactating woman not to breastfeed during treatment with IBRANCE and for 3 weeks after the last dose.

8.3 Females and Males of Reproductive Potential

Pregnancy Testing

Based on animal studies, IBRANCE can cause fetal harm when administered to a pregnant woman [see Use in Specific Populations (8.1)]. Females of reproductive potential should have a pregnancy test prior to starting treatment with IBRANCE.

Contraception

Females

IBRANCE can cause fetal harm when administered to a pregnant woman [see Use in Specific Populations (8.1)]. Advise females of reproductive potential to use effective contraception during treatment with IBRANCE and for at least 3 weeks after the last dose.

Males

Because of the potential for genotoxicity, advise male patients with female partners of reproductive potential to use effective contraception during treatment with IBRANCE and for 3 months after the last dose [see Nonclinical Toxicology (13.1)].

Infertility

Males

Based on animal studies, IBRANCE may impair fertility in males of reproductive potential [see Nonclinical Toxicology (13.1)].

8.4 Pediatric Use

The safety and effectiveness of IBRANCE in pediatric patients have not been established.

The safety and effectiveness of IBRANCE were assessed but not established in three trials: one open-label trial [A5481092, (NCT03709680)] that included 98 pediatric patients 2 to <17 years of age who received IBRANCE in combination with chemotherapy for recurrent or refractory solid tumors and two open-label trials that included 42 pediatric patients 4 to <17 years of age who received IBRANCE as a single agent for recurrent or refractory solid tumors [APEC1621I, (NCT03526250)] or primary central nervous system (CNS) tumors [PBTC-042, (NCT02255461)].

No new safety signals were observed in these trials. Palbociclib exposures in pediatric patients who received IBRANCE as a single agent or in combination were within range of those observed in adults given a similar dose based on body surface area.

Juvenile Animal Toxicity Data

Altered glucose metabolism (glycosuria, hyperglycemia, decreased insulin) associated with changes in the pancreas (islet cell vacuolation), eye (cataracts, lens degeneration), kidney (tubule vacuolation, chronic progressive nephropathy) and adipose tissue (atrophy) were identified in a 27 week repeat-dose toxicology study in rats that were immature at the beginning of the studies and were most prevalent in males at oral palbociclib doses ≥30 mg/kg/day (approximately 11 times the adult human exposure [AUC] at the recommended dose). Some of these findings (glycosuria/hyperglycemia, pancreatic islet cell vacuolation, and kidney tubule vacuolation) were present with lower incidence and severity in a 15 week repeat-dose toxicology study in immature rats. Altered glucose metabolism or associated changes in the pancreas, eye, kidney and adipose tissue were not identified in a 27-week repeat-dose toxicology study in rats that were mature at the beginning of the study and in dogs in repeat-dose toxicology studies up to 39 weeks duration.

Toxicities in teeth independent of altered glucose metabolism were observed in rats. Administration of 100 mg/kg palbociclib for 27 weeks (approximately 15 times the adult human exposure [AUC] at the recommended dose) resulted in abnormalities in growing incisor teeth (discolored, ameloblast degeneration/necrosis, mononuclear cell infiltrate). Other toxicities of potential concern to pediatric patients have not been evaluated in juvenile animals.

8.5 Geriatric Use

Of 444 patients who received IBRANCE in PALOMA-2, 181 patients (41%) were ≥65 years of age and 48 patients (11%) were ≥75 years of age. Of 347 patients who received IBRANCE in PALOMA-3, 86 patients (25%) were ≥65 years of age and 27 patients (8%) were ≥75 years of age. No overall differences in safety or effectiveness of IBRANCE were observed between these patients and younger patients.

8.6 Hepatic Impairment

No dose adjustment is required in patients with mild or moderate hepatic impairment (Child-Pugh classes A and B). For patients with severe hepatic impairment (Child-Pugh class C), the recommended dose of IBRANCE is 75 mg once daily for 21 consecutive days followed by 7 days off treatment to comprise a complete cycle of 28 days [see Dosage and Administration (2.2)]. Based on a pharmacokinetic trial in subjects with varying degrees of hepatic function, the palbociclib unbound exposure (unbound AUCINF) decreased by 17% in subjects with mild hepatic impairment (Child-Pugh class A), and increased by 34% and 77% in subjects with moderate (Child-Pugh class B) and severe (Child-Pugh class C) hepatic impairment, respectively, relative to subjects with normal hepatic function. Peak palbociclib unbound exposure (unbound Cmax) increased by 7%, 38% and 72% for mild, moderate and severe hepatic impairment, respectively, relative to subjects with normal hepatic function [see Clinical Pharmacology (12.3)].

Review the Full Prescribing Information for the aromatase inhibitor or fulvestrant for dose modifications related to hepatic impairment.

8.7 Renal Impairment

No dose adjustment is required in patients with mild, moderate, or severe renal impairment (CrCl >15 mL/min). Based on a pharmacokinetic trial in subjects with varying degrees of renal function, the total palbociclib exposure (AUCINF) increased by 39%, 42%, and 31% with mild (60 mL/min ≤ CrCl <90 mL/min), moderate (30 mL/min ≤ CrCl <60 mL/min), and severe (CrCl <30 mL/min) renal impairment, respectively, relative to subjects with normal renal function. Peak palbociclib exposure (Cmax) increased by 17%, 12%, and 15% for mild, moderate, and severe renal impairment, respectively, relative to subjects with normal renal function. The pharmacokinetics of palbociclib have not been studied in patients requiring hemodialysis [see Clinical Pharmacology (12.3)].

11 DESCRIPTION

IBRANCE capsules for oral administration contain 125 mg, 100 mg, or 75 mg of palbociclib, a kinase inhibitor. The molecular formula for palbociclib is C24H29N7O2. The molecular weight is 447.54 daltons. The chemical name is 6-acetyl-8-cyclopentyl-5-methyl-2-{[5-(piperazin-1-yl)pyridin-2-yl]amino}pyrido[2,3-d]pyrimidin-7(8H)-one, and its structural formula is:

Palbociclib is a yellow to orange powder with pKa of 7.4 (the secondary piperazine nitrogen) and 3.9 (the pyridine nitrogen). At or below pH 4, palbociclib behaves as a high-solubility compound. Above pH 4, the solubility of the drug substance reduces significantly.

Inactive ingredients: Microcrystalline cellulose, lactose monohydrate, sodium starch glycolate, colloidal silicon dioxide, magnesium stearate, and hard gelatin capsule shells. The light orange, light orange/caramel, and caramel opaque capsule shells contain gelatin, red iron oxide, yellow iron oxide, and titanium dioxide; the printing ink contains shellac, titanium dioxide, ammonium hydroxide, propylene glycol, and simethicone.

12 CLINICAL PHARMACOLOGY

12.1 Mechanism of Action

Palbociclib is an inhibitor of cyclin-dependent kinases (CDK) 4 and 6. Cyclin D1 and CDK4/6 are downstream of signaling pathways which lead to cellular proliferation. In vitro, palbociclib reduced cellular proliferation of estrogen receptor (ER)-positive breast cancer cell lines by blocking progression of the cell from G1 into S phase of the cell cycle. Treatment of breast cancer cell lines with the combination of palbociclib and antiestrogens leads to decreased retinoblastoma (Rb) protein phosphorylation resulting in reduced E2F expression and signaling, and increased growth arrest compared to treatment with each drug alone. In vitro treatment of ER-positive breast cancer cell lines with the combination of palbociclib and antiestrogens led to increased cell senescence compared to each drug alone, which was sustained for up to 6 days following palbociclib removal and was greater if antiestrogen treatment was continued. In vivo studies using a patient-derived ER-positive breast cancer xenograft model demonstrated that the combination of palbociclib and letrozole increased the inhibition of Rb phosphorylation, downstream signaling, and tumor growth compared to each drug alone.

Human bone marrow mononuclear cells treated with palbociclib in the presence or absence of an anti-estrogen in vitro did not become senescent and resumed proliferation following palbociclib withdrawal.

12.2 Pharmacodynamics

Cardiac Electrophysiology

The effect of palbociclib on the QT interval corrected for heart rate (QTc) was evaluated using time-matched electrocardiograms (ECGs) evaluating the change from baseline and corresponding pharmacokinetic data in 77 patients with breast cancer. Palbociclib had no large effect on QTc (i.e., >20 ms) at 125 mg once daily for 21 consecutive days followed by 7 days off treatment to comprise a complete cycle of 28 days.

12.3 Pharmacokinetics

The pharmacokinetics (PK) of palbociclib were characterized in patients with solid tumors including advanced breast cancer and in healthy subjects.

Absorption

The mean maximum observed concentration (Cmax) of palbociclib is generally observed between 6 to 12 hours (time to reach maximum concentration, Tmax) following oral administration. The mean absolute bioavailability of IBRANCE after an oral 125 mg dose is 46%. In the dosing range of 25 mg to 225 mg, the AUC and Cmax increased proportionally with dose in general. Steady state was achieved within 8 days following repeated once daily dosing. With repeated once daily administration, palbociclib accumulated with a median accumulation ratio of 2.4 (range 1.5 to 4.2).

Food effect: Palbociclib absorption and exposure were very low in approximately 13% of the population under the fasted condition. Food intake increased the palbociclib exposure in this small subset of the population, but did not alter palbociclib exposure in the rest of the population to a clinically relevant extent. Therefore, food intake reduced the intersubject variability of palbociclib exposure, which supports administration of IBRANCE with food. Compared to IBRANCE given under overnight fasted conditions, the population average area under the concentration-time curve from zero to infinity (AUCINF) and Cmax of palbociclib increased by 21% and 38%, respectively, when given with high-fat, high-calorie food (approximately 800 to 1000 calories with 150, 250, and 500 to 600 calories from protein, carbohydrate, and fat, respectively), by 12% and 27%, respectively, when given with low-fat, low-calorie food (approximately 400 to 500 calories with 120, 250, and 28 to 35 calories from protein, carbohydrate, and fat, respectively), and by 13% and 24%, respectively, when moderate-fat, standard calorie food (approximately 500 to 700 calories with 75 to 105, 250 to 350 and 175 to 245 calories from protein, carbohydrate, and fat, respectively) was given 1 hour before and 2 hours after IBRANCE dosing.

Distribution

Binding of palbociclib to human plasma proteins in vitro was approximately 85%, with no concentration dependence over the concentration range of 500 ng/mL to 5000 ng/mL. The mean fraction unbound (fu) of palbociclib in human plasma in vivo increased incrementally with worsening hepatic function. There was no obvious trend in the mean palbociclib fu in human plasma in vivo with worsening renal function. The geometric mean apparent volume of distribution (Vz/F) was 2583 L with a coefficient of variation (CV) of 26%.

Metabolism

In vitro and in vivo studies indicated that palbociclib undergoes hepatic metabolism in humans. Following oral administration of a single 125 mg dose of [^14C]palbociclib to humans, the primary metabolic pathways for palbociclib involved oxidation and sulfonation, with acylation and glucuronidation contributing as minor pathways. Palbociclib was the major circulating drug-derived entity in plasma (23%). The major circulating metabolite was a glucuronide conjugate of palbociclib, although it only represented 1.5% of the administered dose in the excreta. Palbociclib was extensively metabolized with unchanged drug accounting for 2.3% and 6.9% of radioactivity in feces and urine, respectively. In feces, the sulfamic acid conjugate of palbociclib was the major drug-related component, accounting for 26% of the administered dose. In vitro studies with human hepatocytes, liver cytosolic and S9 fractions, and recombinant SULT enzymes indicated that CYP3A and SULT2A1 are mainly involved in the metabolism of palbociclib.

Elimination

The geometric mean apparent oral clearance (CL/F) of palbociclib was 63.1 L/hr (29% CV), and the mean (± standard deviation) plasma elimination half-life was 29 (±5) hours in patients with advanced breast cancer. In 6 healthy male subjects given a single oral dose of [^14C]palbociclib, a median of 91.6% of the total administered radioactive dose was recovered in 15 days; feces (74.1% of dose) was the major route of excretion, with 17.5% of the dose recovered in urine. The majority of the material was excreted as metabolites.

Specific Populations

Age, Gender, and Body Weight

Based on a population pharmacokinetic analysis in 183 patients with cancer (50 male and 133 female patients, age range from 22 to 89 years, and body weight range from 37.9 to 123 kg), gender had no effect on the exposure of palbociclib, and age and body weight had no clinically important effect on the exposure of palbociclib.

Hepatic Impairment

Data from a pharmacokinetic trial in subjects with varying degrees of hepatic impairment indicate that palbociclib unbound AUCINF decreased 17% in subjects with mild hepatic impairment (Child-Pugh class A), and increased by 34% and 77% in subjects with moderate (Child-Pugh class B) and severe (Child-Pugh class C) hepatic impairment, respectively, relative to subjects with normal hepatic function. Palbociclib unbound Cmax increased by 7%, 38% and 72% for mild, moderate and severe hepatic impairment, respectively, relative to subjects with normal hepatic function. In addition, based on a population pharmacokinetic analysis that included 183 patients, where 40 patients had mild hepatic impairment based on National Cancer Institute (NCI) classification (total bilirubin ≤ ULN and AST > ULN, or total bilirubin >1.0 to 1.5 × ULN and any AST), mild hepatic impairment had no effect on the exposure of palbociclib, further supporting the findings from the dedicated hepatic impairment study.

Renal Impairment

Data from a pharmacokinetic trial in subjects with varying degrees of renal impairment indicate that palbociclib AUCINF increased by 39%, 42%, and 31% with mild (60 mL/min ≤ CrCl <90 mL/min), moderate (30 mL/min ≤ CrCl <60 mL/min), and severe (CrCl <30 mL/min) renal impairment, respectively, relative to subjects with normal renal function. Peak palbociclib exposure (Cmax) increased by 17%, 12%, and 15% for mild, moderate, and severe renal impairment, respectively, relative to subjects with normal renal function. In addition, based on a population pharmacokinetic analysis that included 183 patients where 73 patients had mild renal impairment and 29 patients had moderate renal impairment, mild and moderate renal impairment had no effect on the exposure of palbociclib. The pharmacokinetics of palbociclib have not been studied in patients requiring hemodialysis.

Drug Interactions

In vitro data indicate that CYP3A and SULT enzyme SULT2A1 are mainly involved in the metabolism of palbociclib. Palbociclib is a weak time-dependent inhibitor of CYP3A following daily 125 mg dosing to steady state in humans. In vitro, palbociclib is not an inhibitor of CYP1A2, 2A6, 2B6, 2C8, 2C9, 2C19, and 2D6, and is not an inducer of CYP1A2, 2B6, 2C8, and 3A4 at clinically relevant concentrations.

CYP3A Inhibitors: Data from a drug interaction trial in healthy subjects (N=12) indicate that coadministration of multiple 200 mg daily doses of itraconazole with a single 125 mg IBRANCE dose increased palbociclib AUCINF and the Cmax by approximately 87% and 34%, respectively, relative to a single 125 mg IBRANCE dose given alone [see Drug Interactions (7.1)].

CYP3A Inducers: Data from a drug interaction trial in healthy subjects (N=15) indicate that coadministration of multiple 600 mg daily doses of rifampin, a strong CYP3A inducer, with a single 125 mg IBRANCE dose decreased palbociclib AUCINF and Cmax by 85% and 70%, respectively, relative to a single 125 mg IBRANCE dose given alone. Data from a drug interaction trial in healthy subjects (N=14) indicate that coadministration of multiple 400 mg daily doses of modafinil, a moderate CYP3A inducer, with a single 125 mg IBRANCE dose decreased palbociclib AUCINF and Cmax by 32% and 11%, respectively, relative to a single 125 mg IBRANCE dose given alone [see Drug Interactions (7.2)].

CYP3A Substrates: Palbociclib is a weak time-dependent inhibitor of CYP3A following daily 125 mg dosing to steady state in humans. In a drug interaction trial in healthy subjects (N=26), coadministration of midazolam with multiple doses of IBRANCE increased the midazolam AUCINF and the Cmax values by 61% and 37%, respectively, as compared to administration of midazolam alone [see Drug Interactions (7.3)].

Gastric pH Elevating Medications: In a drug interaction trial in healthy subjects, coadministration of a single 125 mg dose of IBRANCE with multiple doses of the proton pump inhibitor (PPI) rabeprazole under fed conditions decreased palbociclib Cmax by 41%, but had limited impact on AUCINF (13% decrease), when compared to a single dose of IBRANCE administered alone. Given the reduced effect on gastric pH of H2-receptor antagonists and local antacids compared to PPIs, the effect of these classes of acid-reducing agents on palbociclib exposure under fed conditions is expected to be minimal. Under fed conditions there is no clinically relevant effect of PPIs, H2-receptor antagonists, or local antacids on palbociclib exposure. In another healthy subject study, coadministration of a single dose of IBRANCE with multiple doses of the PPI rabeprazole under fasted conditions decreased palbociclib AUCINF and Cmax by 62% and 80%, respectively, when compared to a single dose of IBRANCE administered alone.

Effect of Palbociclib on Transporters: In vitro evaluations indicated that palbociclib has a low potential to inhibit the activities of drug transporters organic anion transporter (OAT)1, OAT3, organic cation transporter (OCT)2, and organic anion transporting polypeptide (OATP)1B1, OATP1B3 at clinically relevant concentrations. In vitro, palbociclib has the potential to inhibit OCT1 at clinically relevant concentrations, as well as the potential to inhibit P-glycoprotein (P-gp) or breast cancer resistance protein (BCRP) in the gastrointestinal tract at the proposed dose.

Effect of Transporters on Palbociclib: Based on in vitro data, P-gp and BCRP mediated transport are unlikely to affect the extent of oral absorption of palbociclib at therapeutic doses.

13 NONCLINICAL TOXICOLOGY

13.1 Carcinogenesis, Mutagenesis, Impairment of Fertility

Palbociclib was assessed for carcinogenicity in a 6-month transgenic mouse study and in a 2-year rat study. Oral administration of palbociclib for 2 years resulted in an increased incidence of microglial cell tumors in the central nervous system of male rats at a dose of 30 mg/kg/day (approximately 8 times the human clinical exposure based on AUC). There were no neoplastic findings in female rats at doses up to 200 mg/kg/day (approximately 5 times the human clinical exposure based on AUC). Oral administration of palbociclib to male and female rasH2 transgenic mice for 6 months did not result in increased incidence of neoplasms at doses up to 60 mg/kg/day.

Palbociclib was aneugenic in Chinese Hamster Ovary cells in vitro and in the bone marrow of male rats at doses ≥100 mg/kg/day for 3 weeks. Palbociclib was not mutagenic in an in vitro bacterial reverse mutation (Ames) assay and was not clastogenic in the in vitro human lymphocyte chromosome aberration assay.

In a fertility study in female rats, palbociclib did not affect mating or fertility at any dose up to 300 mg/kg/day (approximately 4 times human clinical exposure based on AUC) and no adverse effects were observed in the female reproductive tissues in repeat-dose toxicity studies up to 300 mg/kg/day in the rat and 3 mg/kg/day in the dog (approximately 6 times and similar to human exposure [AUC], at the recommended dose, respectively).

The adverse effects of palbociclib on male reproductive function and fertility were observed in the repeat-dose toxicology studies in rats and dogs and a male fertility study in rats. In repeat-dose toxicology studies, palbociclib-related findings in the testis, epididymis, prostate, and seminal vesicle at ≥30 mg/kg/day in rats and ≥0.2 mg/kg/day in dogs included decreased organ weight, atrophy or degeneration, hypospermia, intratubular cellular debris, and decreased secretion. Partial reversibility of male reproductive organ effects was observed in the rat and dog following a 4- and 12-week non-dosing period, respectively. These doses in rats and dogs resulted in approximately ≥10 and 0.1 times, respectively, the exposure [AUC] in humans at the recommended dose. In the fertility and early embryonic development study in male rats, palbociclib caused no effects on mating but resulted in a slight decrease in fertility in association with lower sperm motility and density at 100 mg/kg/day with projected exposure levels [AUC] of 20 times the exposure in humans at the recommended dose.

14 CLINICAL STUDIES

PALOMA-2: IBRANCE plus Letrozole

Patients with ER-positive, HER2-negative advanced or metastatic breast cancer for initial endocrine-based therapy

PALOMA-2 was an international, randomized, double-blind, parallel-group, multicenter study of IBRANCE plus letrozole versus placebo plus letrozole conducted in postmenopausal women with ER-positive, HER2-negative advanced breast cancer who had not received previous systemic treatment for their advanced disease. A total of 666 patients were randomized 2:1 to IBRANCE plus letrozole or placebo plus letrozole. Randomization was stratified by disease site (visceral versus non-visceral), disease-free interval (de novo metastatic versus ≤12 months from the end of adjuvant treatment to disease recurrence versus >12 months from the end of adjuvant treatment to disease recurrence), and nature of prior (neo)adjuvant anticancer therapies (prior hormonal therapies versus no prior hormonal therapy). IBRANCE was given orally at a dose of 125 mg daily for 21 consecutive days followed by 7 days off treatment. Patients received study treatment until objective disease progression, symptomatic deterioration, unacceptable toxicity, death, or withdrawal of consent, whichever occurred first. The major efficacy outcome of the study was investigator-assessed progression-free survival (PFS) evaluated according to Response Evaluation Criteria in Solid Tumors Version 1.1 (RECIST). Additional efficacy outcome measures were confirmed overall response rate (ORR) as assessed by the investigator according to RECIST Version 1.1 and overall survival (OS).

Patients enrolled in this study had a median age of 62 years (range 28 to 89). The majority of patients were White (78%), and most patients had an Eastern Cooperative Oncology Group (ECOG) performance status (PS) of 0 or 1 (98%). Forty-eight percent of patients had received chemotherapy and 56% had received antihormonal therapy in the neoadjuvant or adjuvant setting prior to their diagnosis of advanced breast cancer. Thirty-seven percent of patients had no prior systemic therapy in the neoadjuvant or adjuvant setting. The majority of patients (97%) had metastatic disease. Twenty-three percent of patients had bone only disease, and 49% of patients had visceral disease.

Major efficacy results from PALOMA-2 are summarized in Table 10 and Figure 1. Consistent results were observed across patient subgroups of disease-free interval (DFI), disease site, and prior therapy. The treatment effect of the combination on PFS was also supported by an independent review of radiographs. Based on the prespecified final OS analysis conducted after 435 events, OS was not statistically significant.

Table 10. Efficacy Results – PALOMA-2
 | IBRANCE plus Letrozole | Placebo plus Letrozole
Progression-free survival for ITT (investigator assessment) | N=444 | N=222
Number of PFS events (%) | 194 (43.7) | 137 (61.7)
Median progression-free survival (months, 95% CI) | 24.8 (22.1, NE) | 14.5 (12.9, 17.1)
Hazard ratio (95% CI) and p-value | 0.576 (0.463, 0.718) [Cox proportional hazards model stratified by disease site (visceral vs. non-visceral) per randomization.] , p<0.0001 [Stratified log-rank test one-sided p-value.]
Objective Response for patients with measurable disease (investigator assessment) | N=338 | N=171
Objective response rate [Response is based on confirmed responses.] (%, 95% CI) | 55.3 (49.9, 60.7) | 44.4 (36.9, 52.2)
Overall survival for ITT | N=444 | N=222
Number of OS events (%) | 287 (64.6) | 148 (66.7)
Median OS (months, 95% CI) | 53.8 (49.8, 59.2) | 49.8 (42.3, 56.4)
Hazard ratio (95% CI) and p‑value | 0.921 (0.755, 1.124), p=0.2087
CI=confidence interval; ITT=Intent-to-Treat; N=number of patients; NE=not estimable; OS=overall survival; PFS=progression-free survival.

Figure 1. Kaplan-Meier Plot of Progression-Free Survival – PALOMA-2 (Investigator Assessment, Intent-to-Treat Population)

LET=letrozole; PAL=palbociclib; PBO=placebo.

PALOMA-3: IBRANCE plus Fulvestrant

Patients with HR-positive, HER2-negative advanced or metastatic breast cancer who have had disease progression on or after prior adjuvant or metastatic endocrine therapy

PALOMA-3 was an international, randomized, double-blind, parallel-group, multicenter study of IBRANCE plus fulvestrant versus placebo plus fulvestrant conducted in women with HR-positive, HER2-negative advanced breast cancer, regardless of their menopausal status, whose disease progressed on or after prior endocrine therapy. A total of 521 pre/postmenopausal women were randomized 2:1 to IBRANCE plus fulvestrant or placebo plus fulvestrant and stratified by documented sensitivity to prior hormonal therapy, menopausal status at study entry (pre/peri versus postmenopausal), and presence of visceral metastases. IBRANCE was given orally at a dose of 125 mg daily for 21 consecutive days followed by 7 days off treatment. Pre/perimenopausal women were enrolled in the study and received the LHRH agonist goserelin for at least 4 weeks prior to and for the duration of PALOMA-3. Patients continued to receive assigned treatment until objective disease progression, symptomatic deterioration, unacceptable toxicity, death, or withdrawal of consent, whichever occurred first. The major efficacy outcome of the study was investigator-assessed PFS evaluated according to RECIST 1.1.

Patients enrolled in this study had a median age of 57 years (range 29 to 88). The majority of patients on study were White (74%), all patients had an ECOG PS of 0 or 1, and 80% were postmenopausal. All patients had received prior systemic therapy, and 75% of patients had received a previous chemotherapy regimen. Twenty-five percent of patients had received no prior therapy in the metastatic disease setting, 60% had visceral metastases, and 23% had bone only disease.

The results from the investigator-assessed PFS and final OS from PALOMA-3 are summarized in Table 11. The relevant Kaplan-Meier plots are shown in Figures 2 and 3, respectively. Consistent PFS results were observed across patient subgroups of disease site, sensitivity to prior hormonal therapy, and menopausal status. After a median follow-up time of 45 months, the final OS results were not statistically significant.

Table 11. Efficacy Results – PALOMA-3
 | IBRANCE plus Fulvestrant | Placebo plus Fulvestrant
Progression-free survival for ITT (investigator assessment) | N=347 | N=174
Number of PFS events (%) | 145 (41.8) | 114 (65.5)
Median PFS (months, 95% CI) | 9.5 (9.2, 11.0) | 4.6 (3.5, 5.6)
Hazard ratio (95% CI) and p-value | 0.461 (0.360, 0.591), p<0.0001
Objective Response for patients with measurable disease (investigator assessment) | N=267 | N=138
Objective response rate [Responses are based on confirmed responses.] (%, 95% CI) | 24.6 (19.6, 30.2) | 10.9 (6.2, 17.3)
Overall survival for ITT | N=347 | N=174
Number of OS events (%) | 201 (57.9) | 109 (62.6)
Median OS (months, 95% CI) | 34.9 (28.8, 40.0) | 28.0 (23.6, 34.6)
Hazard ratio (95% CI) and p-value | 0.814 (0.644, 1.029), p=0.0857 [Not statistically significant at the pre-specified 2-sided alpha level of 0.047.] [2-sided p-value from the log-rank test stratified by the presence of visceral metastases and sensitivity to prior endocrine therapy per randomization.]
CI=confidence interval; ITT=Intent-to-Treat; N=number of patients; OS=overall survival; PFS=progression-free survival.

Figure 2. Kaplan-Meier Plot of Progression-Free Survival – PALOMA-3 (Investigator Assessment, Intent-to-Treat Population)

FUL=fulvestrant; PAL=palbociclib; PBO=placebo.

Figure 3. Kaplan-Meier Plot of Overall Survival (Intent-to-Treat Population) – PALOMA-3

FUL=fulvestrant; PAL=palbociclib; PBO=placebo.

INAVO120: IBRANCE plus Inavolisib and Fulvestrant

Adults with PIK3CA-mutated, HR-positive, HER2-negative, locally advanced or metastatic breast cancer whose disease progressed during or within 12 months of completing adjuvant endocrine therapy and who have not received prior systemic therapy for locally advanced or metastatic disease

INAVO120 (NCT04191499) was a randomized (1:1), double-blind, placebo-controlled trial evaluating the efficacy of inavolisib in combination with IBRANCE and fulvestrant in adult patients with endocrine‑resistant PIK3CA‑mutated, HR-positive, HER2-negative (defined as IHC 0 or 1+, or IHC 2+/ISH-), locally advanced or metastatic breast cancer whose disease progressed during or within 12 months of completing adjuvant endocrine therapy and who have not received prior systemic therapy for locally advanced or metastatic disease. Randomization was stratified by presence of visceral disease (yes or no), endocrine resistance (primary or secondary), and geographic region (North America/Western Europe, Asia, other).

Primary endocrine resistance was defined as relapse while on the first 2 years of adjuvant endocrine therapy (ET) and secondary endocrine resistance was defined as relapse while on adjuvant ET after at least 2 years or relapse within 12 months of completing adjuvant ET.

Patients were required to have a HbA1C <6% and fasting blood glucose <126 mg/dL. The study excluded patients with Type 1 diabetes mellitus or Type 2 diabetes mellitus requiring ongoing anti-hyperglycemic treatment at the start of study treatment.

PIK3CA mutation status was prospectively determined in a central laboratory using the FoundationOne® Liquid CDx assay on plasma-derived circulating tumor DNA (ctDNA) or in local laboratories using various validated polymerase chain reaction (PCR) or next-generation sequencing (NGS) assays on tumor tissue or plasma. All patients were required to provide both a freshly collected pre-treatment blood sample and a tumor tissue sample for central evaluation and determination of PIK3CA mutation(s) status.

Patients received either inavolisib 9 mg (n=161) or placebo (n=164) orally once daily, in combination with IBRANCE 125 mg orally once daily for 21 consecutive days followed by 7 days off treatment to comprise a cycle of 28 days, and fulvestrant 500 mg administered intramuscularly on Cycle 1, Days 1 and 15, and then on Day 1 of every 28-day cycle. Patients received treatment until disease progression or unacceptable toxicity. In addition, all pre/perimenopausal women and men received an LHRH agonist throughout therapy.

The baseline demographic and disease characteristics were: median age 54 years (range: 27 to 79 years); 98% female, of which 39% were pre/perimenopausal; 59% White, 38% Asian, 2.5% Unknown, 0.6% Black or African American; 6% Hispanic or Latino; and ECOG PS of 0 (63%) or 1 (36%). Tamoxifen (57%) and aromatase inhibitors (50%) were the most commonly used adjuvant endocrine therapies. Sixty-four percent of patients were considered to have secondary endocrine resistance. Eighty-three percent of patients had received prior chemotherapy (in the neo/adjuvant setting) and 1.2% of patients had been treated with a CDK4/6 inhibitor.

The major efficacy outcome measure was investigator (INV)-assessed PFS per RECIST version 1.1. Additional efficacy outcome measures included OS, INV-assessed ORR, and INV-assessed duration of response (DOR).

Efficacy results are summarized in Table 12 and Figure 4. INV-assessed PFS results were supported by consistent results from a blinded independent central review (BICR) assessment. At the time of the PFS analysis, OS data were not mature with 30% deaths in the overall population.

Table 12. Efficacy Results in Patients with Locally Advanced or Metastatic Breast Cancer in INAVO120
Efficacy Endpoint | IBRANCE plus Inavolisib and Fulvestrant; N=161 | IBRANCE plus Placebo and Fulvestrant; N=164
Progression-Free Survival [Per RECIST version 1.1.] , [Based on investigator assessment.]
Patients with event (%) | 82 (51) | 113 (69)
Median, months (95% CI) | 15.0 (11.3, 20.5) | 7.3 (5.6, 9.3)
Hazard ratio (95% CI) | 0.43 (0.32, 0.59)
p-value | <0.0001
Objective Response Rate,, [Based on confirmed ORR.]
Patients with CR or PR (%) | 94 (58) | 41 (25)
95% CI | (50, 66) | (19, 32)
Duration of Response
Median DOR, months (95% CI) | 18.4 (10.4, 22.2) | 9.6 (7.4, 16.6)
CI=confidence interval; CR=complete response; DOR=duration of response; N=number of patients; PR=partial response.

Figure 4. Kaplan-Meier Curve for Investigator-Assessed Progression-Free Survival in INAVO120

16 HOW SUPPLIED/STORAGE AND HANDLING

IBRANCE is supplied in the following strengths and package configurations:

IBRANCE Capsules
Package Configuration | Capsule Strength (mg) | NDC | Capsule Description
Bottles of 21 capsules | 125 | NDC 0069-0189-21 | opaque, hard gelatin capsules, size 0, with caramel cap and body, printed with white ink "Pfizer" on the cap, "PBC 125" on the body
Bottles of 21 capsules | 100 | NDC 0069-0188-21 | opaque, hard gelatin capsules, size 1, with caramel cap and light orange body, printed with white ink "Pfizer" on the cap, "PBC 100" on the body
Bottles of 21 capsules | 75 | NDC 0069-0187-21 | opaque, hard gelatin capsules, size 2, with light orange cap and body, printed with white ink "Pfizer" on the cap, "PBC 75" on the body

STORAGE AND HANDLING

Store at 20 °C to 25 °C (68 °F to 77 °F); excursions permitted between 15 °C to 30 °C (59 °F to 86 °F) [see USP Controlled Room Temperature].

17 PATIENT COUNSELING INFORMATION

Advise the patient to read the FDA-approved patient labeling (Patient Information).

Myelosuppression/Infection

- Advise patients to immediately report any signs or symptoms of myelosuppression or infection, such as fever, chills, dizziness, shortness of breath, weakness, or any increased tendency to bleed and/or to bruise [see Warnings and Precautions (5.1)].

Interstitial Lung Disease/Pneumonitis

- Advise patients to immediately report new or worsening respiratory symptoms [see Warnings and Precautions (5.2)].

Drug Interactions

- Grapefruit may interact with IBRANCE. Patients should not consume grapefruit products while on treatment with IBRANCE.
- Inform patients to avoid strong CYP3A inhibitors and strong CYP3A inducers.
- Advise patients to inform their healthcare providers of all concomitant medications, including prescription medicines, over-the-counter drugs, vitamins, and herbal products [see Drug Interactions (7)].

Dosing and Administration

- Advise patients to take IBRANCE with food.
- If the patient vomits or misses a dose, an additional dose should not be taken. The next prescribed dose should be taken at the usual time. IBRANCE capsules should be swallowed whole (do not chew, crush, or open them prior to swallowing). No capsule should be ingested if it is broken, cracked, or otherwise not intact.
- Pre/perimenopausal women treated with IBRANCE should also be treated with LHRH agonists [see Dosage and Administration (2.1)].
- When IBRANCE is used in combination, refer to the other products’ Full Prescribing Information for dosing and administration information [see Dosage and Administration (2.1, 2.2)].

Pregnancy, Lactation, and Infertility

- Embryo-Fetal Toxicity
  - Advise females of reproductive potential of the potential risk to a fetus and to use effective contraception during treatment with IBRANCE therapy and for at least 3 weeks after the last dose. Advise females to inform their healthcare provider of a known or suspected pregnancy [see Warnings and Precautions (5.3) and Use in Specific Populations (8.1 and 8.3)].
  - Advise male patients with female partners of reproductive potential to use effective contraception during treatment with IBRANCE and for at least 3 months after the last dose [see Use in Specific Populations (8.3)].
- Lactation: Advise women not to breastfeed during treatment with IBRANCE and for 3 weeks after the last dose [see Use in Specific Populations (8.2)].
- Infertility: Inform males of reproductive potential that IBRANCE may cause infertility and to consider sperm preservation before taking IBRANCE [see Use in Specific Populations (8.3)].

This product's labeling may have been updated. For full prescribing information, please visit www.pfizer.com. For medical information about IBRANCE, please visit www.pfizermedinfo.com or call 1-800-438-1985.

LAB-0723-14.0

PATIENT INFORMATION
IBRANCE® (EYE-brans)
(palbociclib)
Capsules

What is the most important information I should know about IBRANCE?

IBRANCE may cause serious side effects, including:

Low white blood cell counts (neutropenia). Low white blood cell counts are very common when taking IBRANCE and may cause serious infections that can lead to death. Your healthcare provider should check your white blood cell counts before and during treatment.

If you develop low white blood cell counts during treatment with IBRANCE, your healthcare provider may stop your treatment, decrease your dose, or may tell you to wait to begin your treatment cycle. Tell your healthcare provider right away if you have signs and symptoms of low white blood cell counts or infections such as fever and chills.

Lung problems (pneumonitis). IBRANCE may cause severe or life-threatening inflammation of the lungs during treatment that can lead to death. Tell your healthcare provider right away if you have any new or worsening symptoms, including:

- chest pain
- cough with or without mucus
- trouble breathing or shortness of breath

Your healthcare provider may interrupt or stop treatment with IBRANCE completely if your symptoms are severe.

See "What are the possible side effects of IBRANCE?" for more information about side effects.

What is IBRANCE?

IBRANCE is a prescription medicine used:

In adults to treat hormone receptor (HR)-positive, human epidermal growth factor receptor 2 (HER2)-negative breast cancer that has spread to other parts of the body (metastatic) in combination with:

- an aromatase inhibitor as the first hormonal based therapy, or
- fulvestrant in people with disease progression following hormonal therapy.

In adults with hormone receptor (HR)-positive, human epidermal growth factor receptor 2 (HER2)-negative and with an abnormal phosphatidylinositol-3-kinase catalytic subunit alpha (PIK3CA) gene breast cancer that has spread to nearby tissue or lymph nodes (locally advanced), or to other parts of the body (metastatic) in combination with:

- inavolisib and fulvestrant in people with disease progression during or after adjuvant hormonal therapy.

It is not known if IBRANCE is safe and effective in children.

What should I tell my healthcare provider before taking IBRANCE?

Before taking IBRANCE, tell your healthcare provider about all of your medical conditions, including if you:

- have fever, chills, or any other signs or symptoms of infection.
- have liver or kidney problems.
- have any other medical conditions.
- are pregnant, or plan to become pregnant. IBRANCE can harm your unborn baby.
  - Females who are able to become pregnant should use effective birth control during treatment and for at least 3 weeks after the last dose of IBRANCE. Your healthcare provider may ask you to take a pregnancy test before you start treatment with IBRANCE.
  - Males with female partners who can become pregnant should use effective birth control during treatment with IBRANCE for at least 3 months after the last dose of IBRANCE.
  - Talk to your healthcare provider about birth control methods that may be right for you during this time.
  - If you become pregnant or think you are pregnant, tell your healthcare provider right away.
- are breastfeeding or plan to breastfeed. It is not known if IBRANCE passes into your breast milk. Do not breastfeed during treatment with IBRANCE and for 3 weeks after the last dose.

Tell your healthcare provider about all of the medicines you take, including prescription and over-the-counter medicines, vitamins, and herbal supplements. IBRANCE and other medicines may affect each other causing side effects.

Know the medicines you take. Keep a list of them to show your healthcare provider or pharmacist when you get a new medicine.

How should I take IBRANCE?

- Take IBRANCE exactly as your healthcare provider tells you.
- Take IBRANCE with food.
- IBRANCE should be taken at about the same time each day.
- Swallow IBRANCE capsules whole. Do not chew, crush or open IBRANCE capsules before swallowing them.
- Do not take any IBRANCE capsules that are broken, cracked, or that look damaged.
- Avoid grapefruit and grapefruit products during treatment with IBRANCE. Grapefruit may increase the amount of IBRANCE in your blood.
- Do not change your dose or stop taking IBRANCE unless your healthcare provider tells you.
- If you miss a dose of IBRANCE or vomit after taking a dose of IBRANCE, do not take another dose on that day. Take your next dose at your regular time.
- When IBRANCE is used in combination with inavolisib and fulvestrant, or an aromatase inhibitor, also read the Patient Information for the prescribed products.

What are the possible side effects of IBRANCE?

IBRANCE may cause serious side effects. See "What is the most important information I should know about IBRANCE?"

The most common side effects of IBRANCE when used with either letrozole or fulvestrant include:

- Low red blood cell counts and low platelet counts are common with IBRANCE. Call your healthcare provider right away if you develop any of these symptoms during treatment:

- dizziness
- shortness of breath
- weakness

- bleeding or bruising more easily
- nosebleeds

- infections (see "What is the most important information I should know about IBRANCE?")
- tiredness
- nausea
- sore mouth
- abnormalities in liver blood tests

- diarrhea
- hair thinning or hair loss
- increased blood creatinine

The most common side effects of IBRANCE when used in combination with inavolisib plus fulvestrant include:

- high blood sugar levels leading to excessive thirst and urination
- sore mouth
- diarrhea
- decreased white blood cell counts, red blood cell counts, and platelet counts
- decreased blood levels of calcium, potassium, sodium, and magnesium
- increased creatine blood levels
- tiredness
- abnormalities in liver blood tests
- nausea
- rash
- loss of appetite
- COVID-19 infection
- headache

IBRANCE may cause fertility problems in males. This may affect your ability to father a child. Talk to your healthcare provider about family planning options before starting IBRANCE if this is a concern for you.

Tell your healthcare provider if you have any side effect that bothers you or that does not go away.

These are not all of the possible side effects of IBRANCE.

Call your doctor for medical advice about side effects. You may report side effects to FDA at 1-800-FDA-1088.

How should I store IBRANCE?

- Store IBRANCE at 68 °F to 77 °F (20 °C to 25 °C).

Keep IBRANCE and all medicines out of the reach of children.

General information about the safe and effective use of IBRANCE

Medicines are sometimes prescribed for purposes other than those listed in a Patient Information leaflet. Do not use IBRANCE for a condition for which it was not prescribed. Do not give IBRANCE to other people, even if they have the same symptoms you have. It may harm them. You can ask your pharmacist or healthcare provider for more information about IBRANCE that is written for health professionals.

What are the ingredients in IBRANCE?

Active ingredient: palbociclib

Inactive ingredients: microcrystalline cellulose, lactose monohydrate, sodium starch glycolate, colloidal silicon dioxide, magnesium stearate, and hard gelatin capsule shells.

The light orange, light orange/caramel and caramel opaque capsule shells contain: gelatin, red iron oxide, yellow iron oxide, and titanium dioxide.

The printing ink contains: shellac, titanium dioxide, ammonium hydroxide, propylene glycol, and simethicone.
This product’s labeling may have been updated. For the most recent prescribing information, please visit www.pfizer.com.

LAB-0724-11.0

For more information, go to www.pfizer.com or call 1-800-438-1985.

This Patient Information has been approved by the U.S. Food and Drug Administration. Revised September 2025

PRINCIPAL DISPLAY PANEL - 75 mg Capsule Bottle Label

NDC 0069-0187-21

Pfizer

Ibrance®
(palbociclib)
capsules

75 mg

21 Capsules

Rx only

PRINCIPAL DISPLAY PANEL - 100 mg Capsule Bottle Label

NDC 0069-0188-21

Pfizer

Ibrance®
(palbociclib)
capsules

100 mg

21 Capsules

Rx only

PRINCIPAL DISPLAY PANEL - 125 mg Capsule Bottle Label

NDC 0069-0189-21

Pfizer

Ibrance®
(palbociclib)
capsules

125 mg

21 Capsules

Rx only